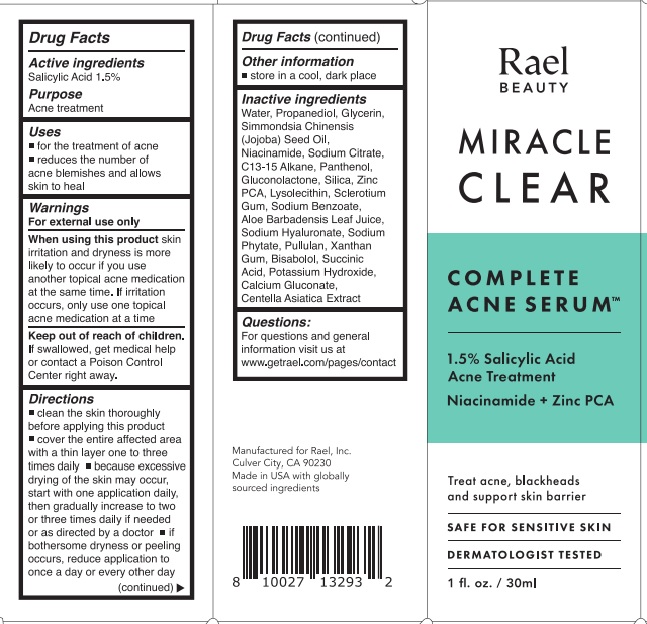 DRUG LABEL: Rael Beauty Miracle Clear Complete Acne Serum
NDC: 64412-1006 | Form: EMULSION
Manufacturer: Twincraft Inc.
Category: otc | Type: HUMAN OTC DRUG LABEL
Date: 20251217

ACTIVE INGREDIENTS: SALICYLIC ACID 15 mg/1 mL
INACTIVE INGREDIENTS: PROPANEDIOL; GLYCERIN; SILICON DIOXIDE; JOJOBA OIL; NIACINAMIDE; PANTHENOL; ZINC PIDOLATE; CAPRYLOYL SALICYLIC ACID; BETASIZOFIRAN; POWDERED CELLULOSE; SODIUM BENZOATE; ALOE VERA LEAF; PULLULAN; XANTHAN GUM; HYALURONATE SODIUM; PHYTATE SODIUM; SUCCINIC ACID; POTASSIUM HYDROXIDE; CALCIUM GLUCONATE; CENTELLA ASIATICA TRITERPENOIDS; WATER; SODIUM CITRATE; OATMEAL; C13-15 ALKANE; GLUCONOLACTONE; LYSOPHOSPHATIDYLCHOLINE, SOYBEAN

Rael Beauty Miracle Clear Complete Acne Serum

Active ingredients

Salicylic Acid 1.5%

Purpose

Acne treatment

Uses

- for the treatment of acne
- reduces the number of acne blemishes and allows skin to heal

Warnings

For external use only

When using this product

skin irritation and dryness is more likely to occur if you use another topical acne medication at the same time. If irritation occurs, only use one topical acne medication at a time.

Keep out of reach of children.

If swallowed, get medical help or contact a Poison Control Center right away.

Directions

- clean the skin thoroughly before applying this product
- cover the entire affected area with a thin layer one to three times daily
- because excessive drying of the skin may occur, start with one application daily, then gradually increase to two or three times daily if needed or as directed by a doctor
- if bothersome dryness or peeling occurs, reduce application to once a day or every other day

Other information

- store in a cool, dark place

Inactive ingredients

Water, Propanediol, Glycerin, Simmondsia Chinensis (Jojoba) Seed Oil, Niacinamide, Sodium Citrate, Avena Sativa (Oat) Kernel Flour, C13-15 Alkane, Panthenol, Gluconolactone, Silica, Lysolecithin, Sclerotium Gum, Cellulose, Zinc PCA, Capryloyl Salicylic Acid, Sodium Benzoate, Aloe Barbadensis Leaf Juice, Pullulan, Xanthan Gum, Sodium Hyaluronate, Sodium Phytate, Succinic Acid, Potassium Hydroxide, Calcium Gluconate, Centella Asiatica Extract

Questions or comments?

(800) 573-1516

Company Information

Manufactured for Rael, Inc. Los Angeles, CA 90012